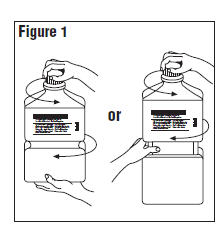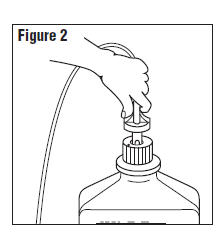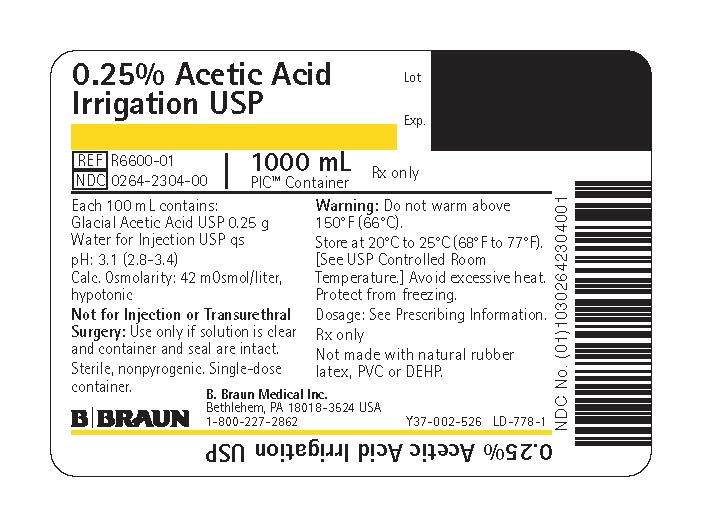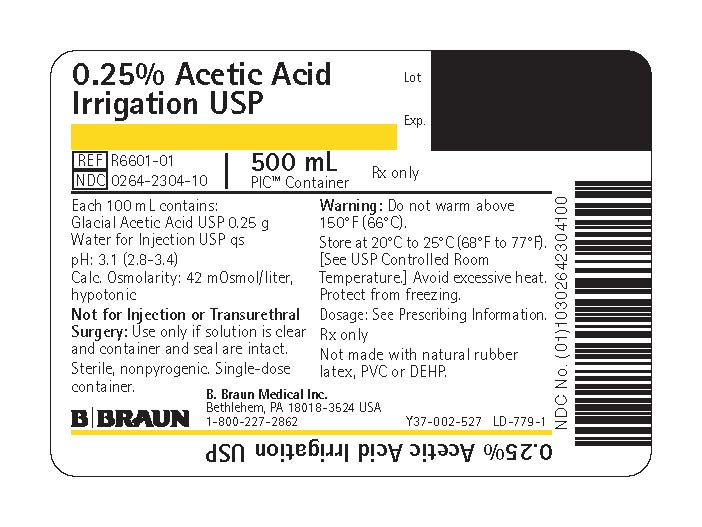 DRUG LABEL: Acetic Acid
NDC: 0264-2304 | Form: IRRIGANT
Manufacturer: B. Braun Medical Inc.
Category: prescription | Type: HUMAN PRESCRIPTION DRUG LABEL
Date: 20230823

ACTIVE INGREDIENTS: ACETIC ACID 0.25 g/100 mL
INACTIVE INGREDIENTS: WATER

0.25% Acetic Acid
Irrigation USP

Package Insert

PIC™ (Plastic Irrigation Containers)

Urologic Irrigating Fluid for Patients Requiring Prolonged
Indwelling Urethral Catheterization.
Not for Transurethral Surgical Procedures.
Not for Injection.

Rx only

DESCRIPTION

Each 100 mL contains:
Glacial Acetic Acid USP 0.25 g
Water for Injection USP qs

pH: 3.1 (2.8-3.4)
Calculated Osmolarity: 42 mOsmol/liter

The formula of the active ingredient is:

Ingredient | Molecular Formula | Molecular Weight
Glacial Acetic Acid USP | CH3COOH | 60.05

0.25% Acetic Acid Irrigation USP is a prediluted, sterile, nonpyrogenic aqueous solution suitable for urologic irrigation. It contains no preservatives or added buffers. The solution is hypotonic.

The plastic container is a copolymer of ethylene and propylene formulated and developed for parenteral drugs. The copolymer contains no plasticizers and exhibits virtually no leachability. The plastic container is also virtually impermeable to vapor transmission and therefore, requires no overwrap to maintain the proper drug concentration. The safety of the plastic container has been confirmed by biological evaluation procedures. The material passes Class Vl testing as specified in the U.S. Pharmacopeia for Biological Tests — Plastic Containers. These tests have shown that the container is nontoxic and biologically inert.

Not made with natural rubber latex, PVC or DEHP.

CLINICAL PHARMACOLOGY

Irrigation of the urinary bladder with acetic acid solution in a concentration of 0.25% has been shown to exert an antimicrobial action against a variety of microorganisms (especially ammonia-forming bacteria) that frequently gain access to the urinary bladder in patients who require prolonged indwelling urethral catheterization. Its antimicrobial action is dependent on administration via the indwelling catheter at a sufficient rate (continuous or intermittent) to maintain an effluent pH of 5.0 or lower. Maintenance of low pH of bladder urine also helps reduce formation of calcium encrustations in the indwelling catheter.

INDICATIONS AND USAGE

0.25% Acetic Acid Irrigation USP is indicated as a constant or intermittent bladder rinse to help prevent the growth and proliferation of susceptible urinary pathogens (especially ammonia-forming bacteria) in the management of patients who require prolonged placement of an indwelling urethral catheter. It also may be used for periodic irrigation of an indwelling catheter to help maintain patency by reducing the formation of calcium encrustations.

CONTRAINDICATIONS

0.25% Acetic Acid Irrigation USP is not for injection.

This solution is contraindicated for irrigation during transurethral surgical procedures.

WARNINGS

FOR UROLOGIC IRRIGATION ONLY. NOT FOR INJECTION.

Use of this solution in patients with mucosal lesions of the urinary bladder may be harmful due to irritation of the lesion. Absorption via open lesions of the bladder mucosa may result in systemic acidosis.

Do not warm above 150°F (66°C).

After opening container, the contents should be used promptly in order to minimize the possibility of bacterial growth or pyrogen formation.

Discard unused portion of irrigating solution since it contains no preservative.

PRECAUTIONS

General

Use aseptic technique when preparing and administering sterile irrigation solutions.

Use only if solution is clear and container and seal are intact.

If pain or hematuria should occur during irrigation, it should be discontinued and the patient reevaluated.

When used for irrigation via appropriate irrigation equipment, the administration set should be attached promptly. Unused portions should be discarded and a fresh container of appropriate size used for the start up of each cycle or repeat procedure. For repeated irrigations of urethral catheters, a separate container should be used for each patient.

Carcinogenesis, Mutagenesis, Impairment of Fertility

Studies with 0.25% Acetic Acid Irrigation USP have not been performed to evaluate carcinogenic potential, mutagenic potential, or effects on fertility.

Pregnancy

Teratogenic Effects

Animal reproduction studies have not been conducted with 0.25% Acetic Acid Irrigation USP. It is also not known whether 0.25% Acetic Acid Irrigation USP can cause fetal harm when administered to a pregnant woman or can affect reproduction capacity. 0.25% Acetic Acid Irrigation USP should be given to a pregnant woman only if clearly needed.

Nursing Mothers

Caution should be exercised when 0.25% Acetic Acid Irrigation USP is administered to a nursing woman.

Pediatric Use

Safety and effectiveness in pediatric patients have not been established.

Geriatric Use

Clinical studies of 0.25% Acetic Acid Irrigation USP have not been performed to determine whether patients over 65 years of age respond differently from younger subjects. Although systemic absorption of the product is unlikely, greater sensitivity of some older individuals cannot be ruled out.

ADVERSE REACTIONS

Systemic acidosis, pain, and hematuria have been reported in patients receiving urinary bladder irrigation with 0.25% acetic acid solution.

If an adverse reaction does occur, discontinue administration of the irrigant, evaluate the patient, institute appropriate therapeutic countermeasures, and save the remainder of the fluid for examination, if deemed necessary.

OVERDOSAGE

Systemic absorption is unlikely unless there are open lesions of the bladder mucosa that have gone undetected. In such event, discontinue the irrigation, evaluate the patient for possible systemic acidosis, intravascular hemolysis, and circulatory overload and institute appropriate countermeasures as indicated. See WARNINGS, PRECAUTIONS, and ADVERSE REACTIONS.

DOSAGE AND ADMINISTRATION

As required for urologic irrigation.

0.25% Acetic Acid Irrigation USP may be administered by gravity drip via an administration set connected to an indwelling urethral catheter designed for continuous or intermittent two-way flow.

For continuous or intermittent irrigation, the rate of administration will correspond roughly to the rate of urine flow and should be adjusted to maintain a urinary effluent pH of 4.5 to 5.0.

Nitrazine or other pH paper may be used to monitor pH, preferably at least four times daily. Drip rate should be adjusted as necessary to maintain desired pH; increasing flow rate reduces pH value and vice versa. With continuous or intermittent irrigation, each patient will require a volume of approximately 500 to 1500 mL per 24 hours.

Some additives may be incompatible. Consult with pharmacist. When introducing additives, use aseptic techniques. Mix thoroughly. Do not store.

This drug product should be inspected visually for particulate matter and discoloration prior to administration, whenever solution and container permit.

HOW SUPPLIED

0.25% Acetic Acid Irrigation USP is supplied sterile and nonpyrogenic in 1000 mL and 500 mL PIC™ (Plastic Irrigation Containers) packaged 16 per case.

NDC | Cat. No. | Size
0.25% Acetic Acid Irrigation USP
0264-2304-00 | R6600-01 | 1000 mL
0264-2304-10 | R6601-01 | 500 mL

STORAGE AND HANDLING

Exposure of pharmaceutical products to heat should be minimized. Avoid excessive heat. Protect from freezing. Store at 20°C to 25°C (68°F to 77°F); excursions permitted between 15°C to 30°C (59°F to 86°F). [See USP Controlled Room Temperature.] However, brief exposure up to 40°C does not adversely affect the product.

Do not warm above 150°F (66°C).

Revised: June 2023

PIC is a trademark of B. Braun Medical Inc.

Directions for Use of PIC™ (Plastic Irrigation Container)

Not for injection.

Aseptic technique is required.

1. Caution – Before use, perform the following checks:
  (a) Read the label. Ensure solution is the one ordered and is within the expiration date.
  (b) Invert container and inspect the solution in good light for cloudiness, haze, or particulate matter; check the container for leakage or damage. Any container which is suspect should not be used.
  Use only if solution is clear and container and seal are intact.
  Single-dose container. Discard unused portion.
2. Outer Closure Removal – Grasp the container with one hand and turn the breakaway ring counterclockwise with the other hand until slight resistance is felt. Then, twisting the container in the opposite direction, turn the breakaway ring sharply until the entire outer cap is loose and can be lifted off. (Figure 1)
3. Connect the administration set through the sterile set port according to set instructions (Figure 2) or remove screw cap and pour.
4. Do not warm above 150°F (66°C) to assure minimal bottle distortion. Keep bottles upright.

B. Braun Medical Inc.
Bethlehem, PA 18018-3524 USA
1-800-227-2862

Y36-002-964 LD-777-1

PRINCIPAL DISPLAY PANEL - 1000 mL Bag Label

0.25% Acetic Acid
Irrigation USP

REF R6600-01
NDC 0264-2304-00
1000 mL

PIC™ Container

Rx only

Each 100 mL contains:
Glacial Acetic Acid USP 0.25 g
Water for Injection USP qs

pH: 3.1 (2.8–3.4)
Calc. Osmolarity: 42 mOsmol/liter, hypotonic

Not for Injection or Transurethral Surgery: Use only if solution is clear and container and seal are intact.

Sterile, nonpyrogenic. Single-dose container.

Warning: Do not warm above 150°F (66°C).

Store at 20°C to 25°C (68°F to 77°F). [See USP Controlled Room Temperature.] Avoid excessive heat. Protect from freezing.

Dosage: See Prescribing Information.

Rx only

Not made with natural rubber latex, PVC or DEHP.

B. Braun Medical Inc.
Bethlehem, PA 18018-3524 USA
1-800-227-2862

Lot
Exp.

Y37-002-526 LD-778-1

0.25% Acetic Acid Irrigation USP

PRINCIPAL DISPLAY PANEL - 500 mL Bag Label

0.25% Acetic Acid
Irrigation USP

REF R6601-01
NDC 0264-2304-10
500 mL

PIC™ Container

Rx only

Each 100 mL contains:
Glacial Acetic Acid USP 0.25 g
Water for Injection USP qs

pH: 3.1 (2.8–3.4)
Calc. Osmolarity: 42 mOsmol/liter, hypotonic

Not for Injection or Transurethral Surgery: Use only if solution is clear and container and seal are intact.

Sterile, nonpyrogenic. Single-dose container.

Warning: Do not warm above 150°F (66°C).

Store at 20°C to 25°C (68°F to 77°F). [See USP Controlled Room Temperature.] Avoid excessive heat. Protect from freezing.

Dosage: See Prescribing Information.

Rx only

Not made with natural rubber latex, PVC or DEHP.

B. Braun Medical Inc.
Bethlehem, PA 18018-3524 USA
1-800-227-2862

Lot
Exp.

Y37-002-527 LD-779-1

0.25% Acetic Acid Irrigation USP